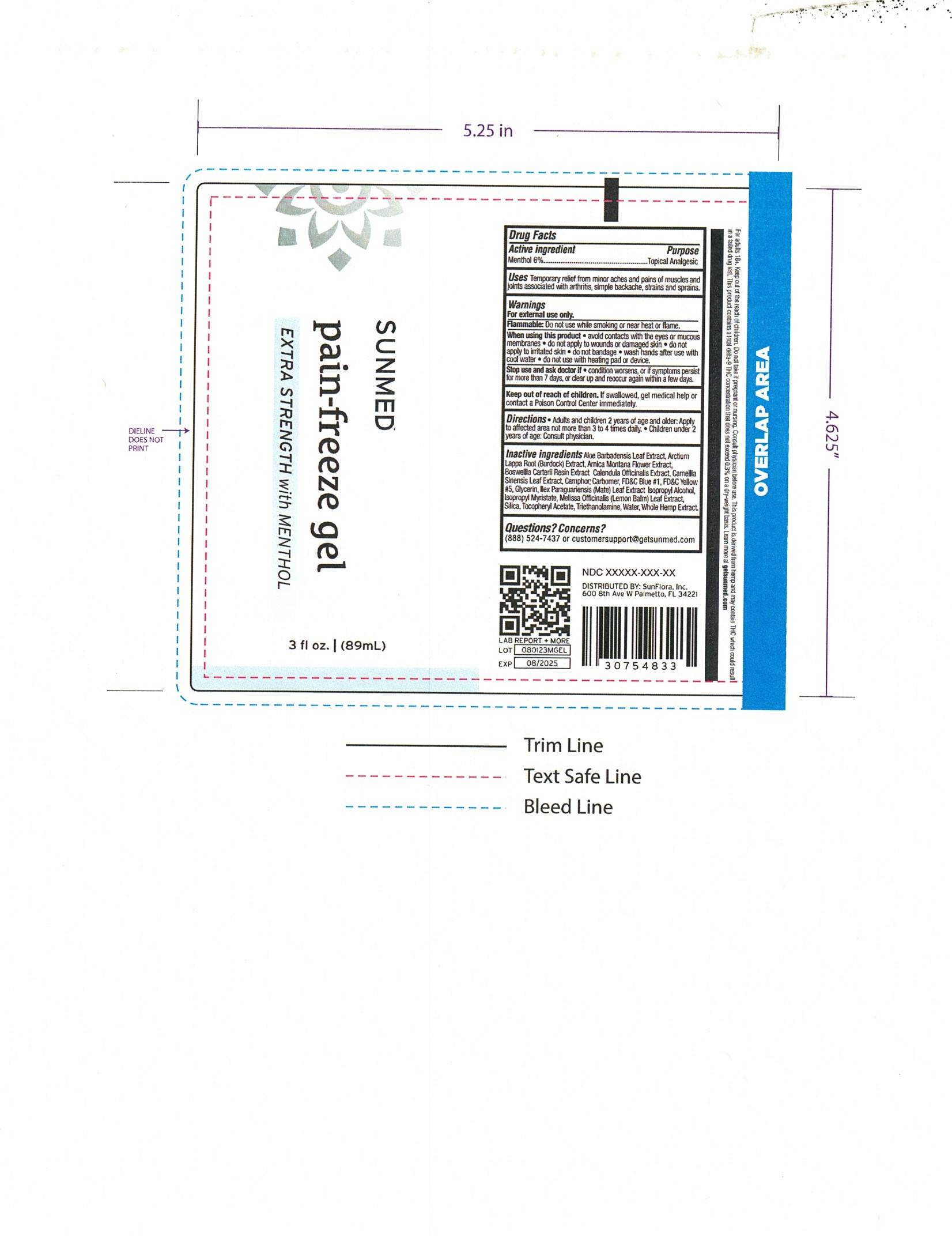 DRUG LABEL: SUNMED pain freeze
NDC: 73240-904 | Form: SPRAY
Manufacturer: Sunflora Inc.
Category: otc | Type: HUMAN OTC DRUG LABEL
Date: 20250819

ACTIVE INGREDIENTS: MENTHOL 6 g/100 mL
INACTIVE INGREDIENTS: CALENDULA OFFICINALIS WHOLE; CAMPHOR (NATURAL); CARBOMER 980; ILEX PARAGUARIENSIS LEAF; MELISSA OFFICINALIS LEAF; PHENOXYETHANOL; ALOE VERA LEAF; CANNABIDIOL; GLYCERIN; ISOPROPYL ALCOHOL; CAMELLIA SINENSIS WHOLE; FRANKINCENSE; FD&C BLUE NO. 1; FD&C YELLOW NO. 5; ISOPROPYL MYRISTATE; .ALPHA.-TOCOPHEROL ACETATE; TROLAMINE; WATER; ARCTIUM LAPPA ROOT; ARNICA MONTANA FLOWER; SILICON DIOXIDE

SUNMED pain spray Fast-Acting with MENTHOL

ACTIVE INGREDIENT

Menthol ................ 6%

PURPOSE

Topical Analgesic

INDICATIONS AND USAGE

Temporary relief from minor aches and pains of muscles and joints associated with arthritis,simple backache,strains and sprains.

WARNINGS

For external use only

When using this product • avoid contacts with the eyes Of mucous membranes • do not apply to wounds or damaged skin • do not apply to irritated skin • do not bandage • wash hands after use with cool water • do not use with heating pad or device.

Stop use and ask doctor if condition worsens or symptoms persist for more than 7 days, or clear up and reoccur a gain within few days.

Keep out of reach of children.If swallowed, get medical help or contact a Poison Control Center immediately

DOSAGE AND ADMINISTRATION

Directions: Adult and children 2 years of age and older. Apply to affected area not more than 3 to 4 times daily. Children under 2 years of age consult a physician

INACTIVE INGREDIENT

Inactive ingredients /Joo Barbadensis Leaf Extract,Arcium Lappa Roof (Buroock) Extract, Amica Montana Flower Extract, Boswellia Carteni Resin Extract Calendu Officinalis Extract, Camellia Sinensis Leaf Extract,Camphor; CartJomer,FD&C Blue #1,FD&C Yellow #5,Glycenn,llex Paraguanensis (Mate) Leaf Extract oopropyf /Jcoh , oopropyf Myristafe,Melissa Officinalis (LemooBalm)Leaf Extract, Silica,T=heryf Acetate,Tnethanolamine,water,Whole Hemp Extract